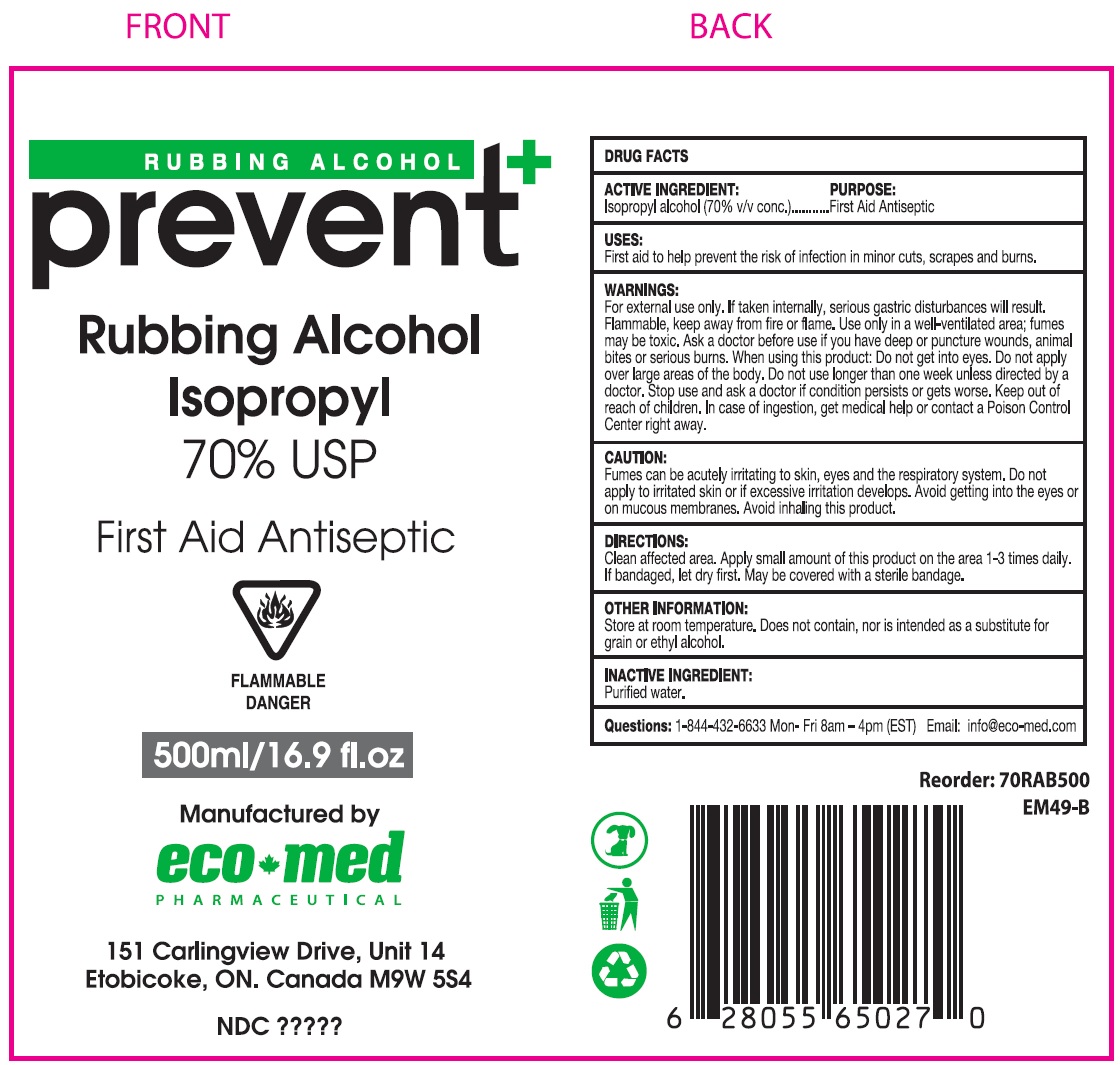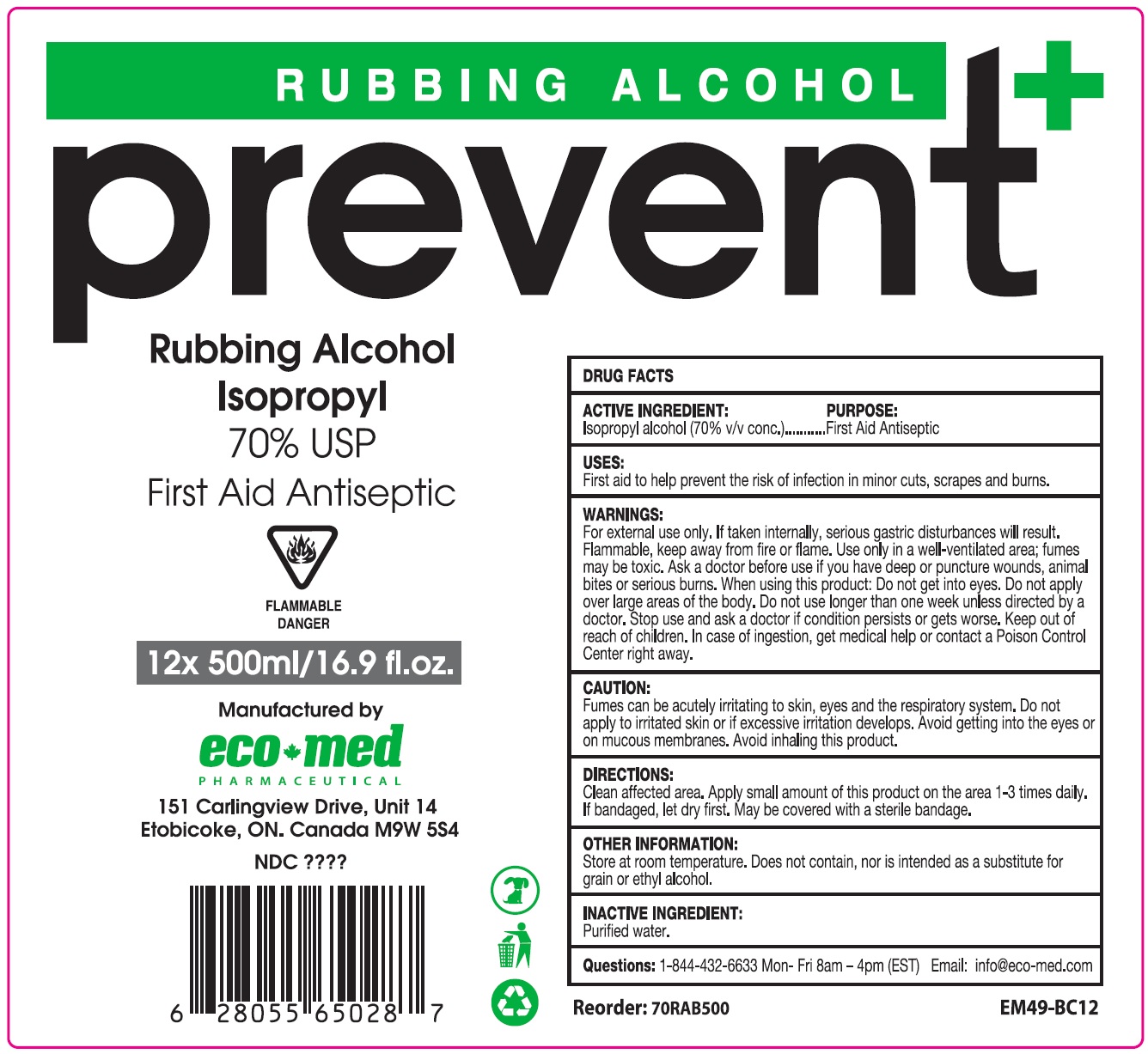 DRUG LABEL: Prevent Rubbing Alcohol Isopropyl 70 Percent
NDC: 78835-006 | Form: LIQUID
Manufacturer: Eco-Med Pharmaceuticals, Inc.
Category: otc | Type: HUMAN OTC DRUG LABEL
Date: 20201029

ACTIVE INGREDIENTS: ISOPROPYL ALCOHOL 0.7 mL/1 mL
INACTIVE INGREDIENTS: WATER

Prevent+ Rubbing Alcohol Isopropyl 70% USP

ACTIVE INGREDIENT

Isopropyl alcohol (70% v/v conc.)

PURPOSE:

First Aid Antiseptic

USES:

First aid to help prevent the risk of infection in minor cuts, scrapes and burns.

WARNINGS:

For external use only. If taken internally, serious gastric disturbances will result.

Flammable, keep away from fire or flame. Use only in a well-ventillated area; fumes may be toxic.

Ask a doctor before use

if you have deep or puncture wounds, animal bites or serious burns,

When using this product:

Do not get into eyes. Do not apply over large areas of the body.

Do not use

longer than one week unless directed by a doctor.

Stop use and ask a doctor

if condition persists or gets worse.

Keep out of reach of children.

In case of ingestion, get medical help or contact a Poison Control Center right away.

CAUTION:

Fumes can be acutely irritating to skin, eyes and the respiratory system. Do not apply to irritated skin or if excessive irritation develops. Avoid getting into the eyes or on mucous membranes. Avoid inhaling this product.

DIRECTIONS:

Clean affected area. Apply small amount of this product on the area 1-3 times daily. If bandaged, let dry first. May be covered with a sterile bandage.

OTHER INFORMATION:

Store at room temperature. Does not contain, nor is intended as a substitute for grain or ethyl alcohol.

INACTIVE INGREDIENT:

Purified water.

Questions:

1-844-432-6633 Mon- Fri 8am - 4 pm (EST) Email: info@eco-med.com